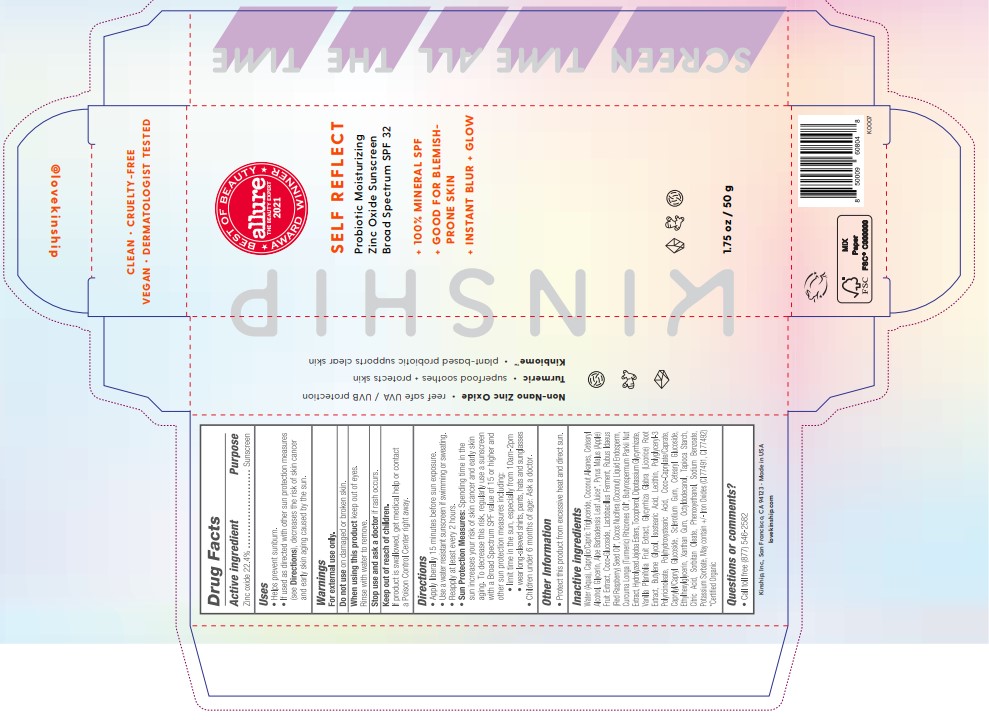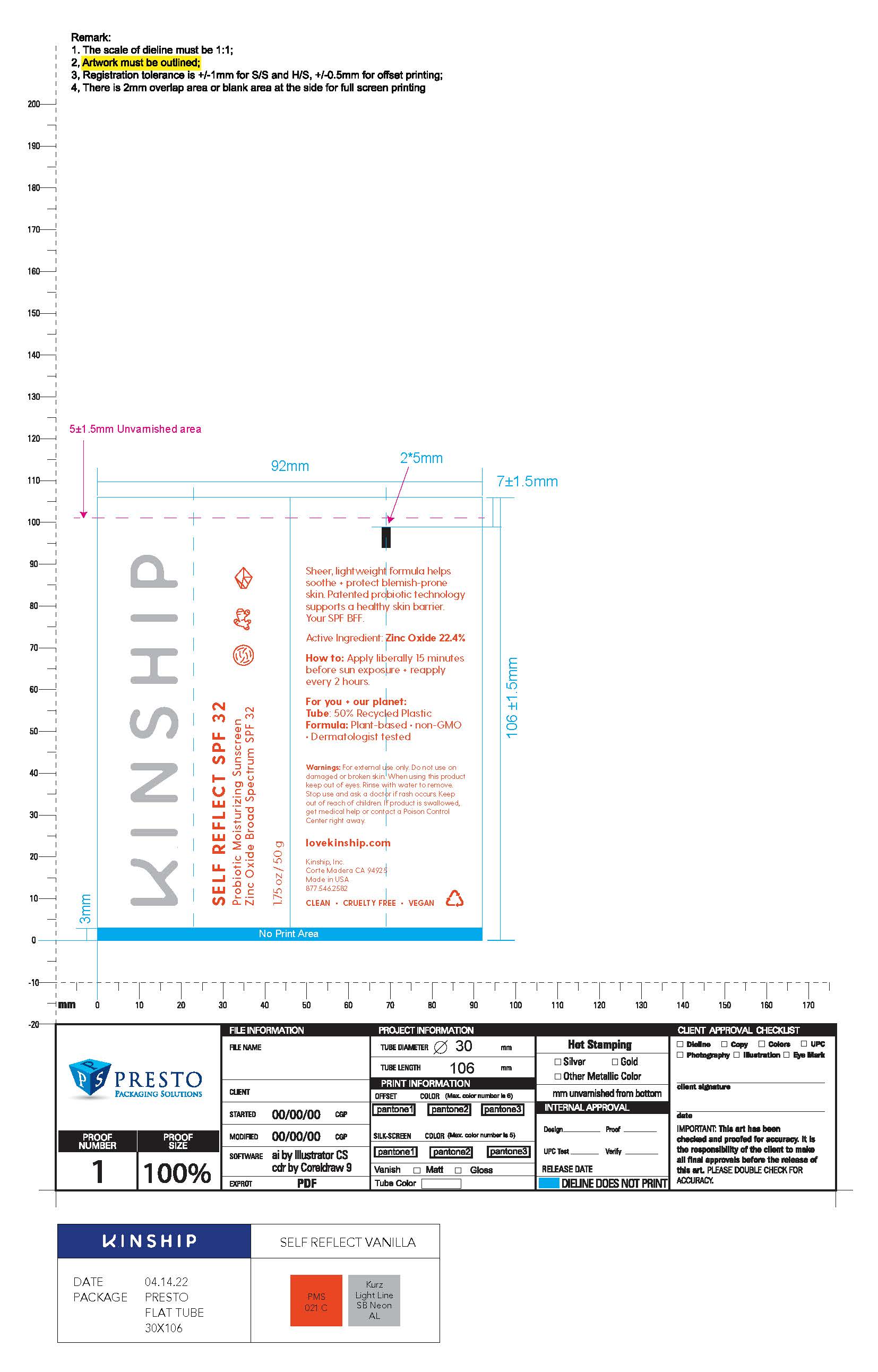 DRUG LABEL: Cream
NDC: 61354-115 | Form: CREAM
Manufacturer: Oxygen Development LLC
Category: otc | Type: HUMAN OTC DRUG LABEL
Date: 20231026

ACTIVE INGREDIENTS: ZINC OXIDE 21.76 mg/100 mg
INACTIVE INGREDIENTS: POLYGLYCERYL-3 PENTARICINOLEATE 0.96 mg/100 mg; WATER 36.09 mg/100 mg; APPLE 1.5 mg/100 mg; COCO GLUCOSIDE 1.05 mg/100 mg; POLYHYDROXYSTEARIC ACID (2300 MW) 0.96 mg/100 mg; LECITHIN, SUNFLOWER 0.96 mg/100 mg; MEDIUM-CHAIN TRIGLYCERIDES 16.85 mg/100 mg; COCONUT ALKANES 4.7 mg/100 mg; RASPBERRY SEED OIL 0.49 mg/100 mg; PHENOXYETHANOL 0.9 mg/100 mg; LACTOBACILLUS REUTERI F275 STRAIN 0.99 mg/100 mg; GLYCERIN 4.79 mg/100 mg; CETOSTEARYL ALCOHOL 4.22 mg/100 mg; ISOSTEARIC ACID 0.96 mg/100 mg

Self Reflect Probiotic Moisturizing Zinc Oxide Sunscreen Broad Spectrum SPF 32

Active ingredient

Zinc Oxide 22.4%

Purpose

Sunscreen

Uses

Help prevent sunburn.

If used as directed with other sun protection measures (see Directions), decreases the risk of skin cancer and early skin agung caused by the sun.

Warnings

For external use only.

Do not use on damaged or broken skin.

When using this product keep out of eyes.

Rinse with water to remove.

Stop use and ask a doctor if rash occurs.

Keep out of reach of children

If product is swallowed, get medical help or contact a Poison Control Center right away.

Directions

Apply liberally 15 minutes before sun exposure.

Use water resistant sunscreen if swimming or sweating.

Reapply at least every 2 hours.

Sun protection measures:

Spending time in the sun increases this risk, regularly use a sunscreen with a Broad Spectrum SPF value of 15 or higher and other sun protection measures including:

-limit time in the sun, especially from 10 am-2 pm.

-wear long-sleeved shirts, pants, hats and sunglasses.

-children under 6 months of age: Ask a doctor.

Other information

Protect this product from excessive heat and direct sun.

Inactive ingredients

Water(Aqua), Caprylic/Capric Triglyceride, Coconut Alkanes, Cetearyl Alcohol, Glycerin, Aloe Barbadensis Leaf Juice*, Pyrus Malus (Apple) Fruit Extract, Coco-Glucoside, Lactobacillus Ferment, Rubus Idaeus (Raspberry) Seed Oil, Cocos Nucifera (Coconut) Liquid Endosperm, Curcuma Longa (Turmeric) Rhizomes Oil, Butyrospermum Parkii Nut Extract, Hydrolyzed Jojoba Esters, Tocopherol, Dipotassium Glycyrrhizinate, Vanilla Planifolia Fruit Extract, Glycyrrhiza Glabra (Licorice) Root Extract, Butylene Glycol, Isostearic Acid, Lecithin, Polyglyceryl-3 Polyricinoleate, Polyhydroxystearic Acid, Coco-Caprylate/Caprate, Caprylyl/Capryl Glucoside, Glucoside, Sclerotium Gum, Cetearyl Glucoside, Ethylhexylglycerin, Xanthan Gum, Octyldodecanol, Tapioca Starch, Citric Acid, Sorbitan Oleate, Phenoxyethanol, Sodium Benzoate, Potassium Sorbate, May contain +/- Iron Oxides (CI 77491, CI 77492) *Certified Organic.